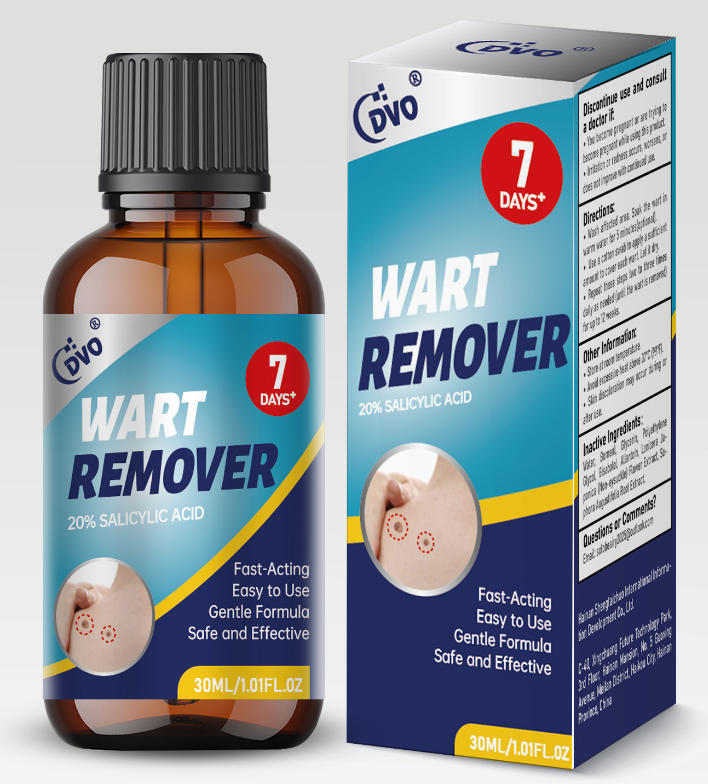 DRUG LABEL: DVO  WART REMOVER
NDC: 87204-162 | Form: LIQUID
Manufacturer: Guangzhou Huixue Biotechnology Co., Ltd.
Category: otc | Type: HUMAN OTC DRUG LABEL
Date: 20260130

ACTIVE INGREDIENTS: SALICYLIC ACID 6 mg/30 g
INACTIVE INGREDIENTS: GLYCERIN; WATER; BORNEOL; BISABOLOL; ALLANTOIN

ACTIVE INGREDIENT

Salicylic Acid 20% V/V

INACTIVE INGREDIENT

Water, Borneol, Glycerin, Polyethylene Glycol, Bisabolol, Allantoin, Lonicera Japonica (Non-eysuckle) Flower Extract, Sophora Augustifolia Root Extract.

PURPOSE

Wart remover

INDICATIONS AND USAGE

For the removal of warts, including plantar warts, flat warts, common warts, corns, and calluses.

Wash affected area, Soak the wart in warm water for 5 minutes(optional). Use a cotton swab to apply a sufficient amount to cover each wart, Let it dry. Repeat these steps two to three times daily as needed (until the wart is removed) for up to 12 weeks.

WARNINGS

Foexternal use only Flammrable, Keen away from fire and flame. Keep out of reach of children. Avoid contact with eyes. In case of contact, flush eyes with glenty of cool water. Do not swallow. If swatowed, seek medieol ottention or contactPeioon Gontret Center (1-800-222-1222) immediataly.

Children should use this product under adult supervision .

If swallowed, get medical help or contact a Poison Control Center right away.

WHEN USING

Fosexternal use only Flammable. Keep away from fire and flame. Keep out oreach of children Avoid contact with eyes. In case of contact, flush eyes withglenty of cool water. . Do not swallow. If swatowed, seek medielottentien orconteetionGontret Center (1-800-222-1222) immediately. Other Warnings Children should use this product under adult supervision, Avoid prolonged exposure to air during use as the substance may dissolve and crystallize easily. • Recap immediately after each use. Do not use if the cap is broken or missing.

DO NOT USE

On irritated skin or on any area that is infected or reddened. • If you are allergic to any ingredient in this product . On moles, birthmarks, warts with hair growing from them, genital warts or warts on the face or mucous membranes. yhavediabetespoorod ccuation, . If you are pregnant or breastfeeding unless directed by a healthcare practitioner.

STOP USE

Discontinue use and consult a doctor if: .You become pregnant or are trying to become pregnant while using this product. • Irritation or redness occurs, worsens, or does not improve with continued use.

DOSAGE AND ADMINISTRATION

Twice each day, (1ml)each time. 15 days supply